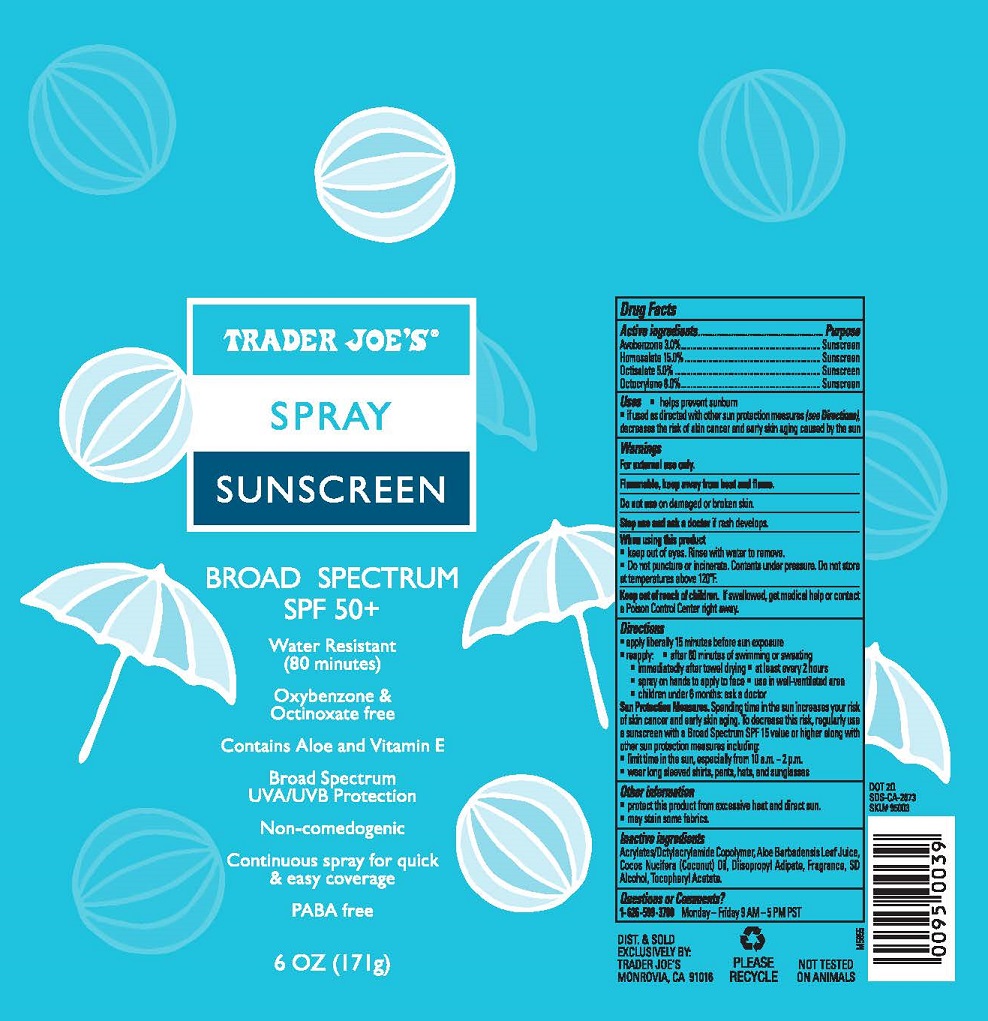 DRUG LABEL: TRADER JOES SUNSCREEN

NDC: 71270-154 | Form: SPRAY
Manufacturer: Trader Joe's Company
Category: otc | Type: HUMAN OTC DRUG LABEL
Date: 20251222

ACTIVE INGREDIENTS: AVOBENZONE 3 g/100 g; HOMOSALATE 15 g/100 g; OCTISALATE 5 g/100 g; OCTOCRYLENE 8 g/100 g
INACTIVE INGREDIENTS: OCTYL ACRYLATE; ALOE VERA LEAF; COCONUT OIL; DIISOPROPYL ADIPATE; ALCOHOL; .ALPHA.-TOCOPHEROL ACETATE

TRADER JOE’S (as PLD) - SPRAY SUNSCREEN SPF 50+ (71270-154)

ACTIVE INGREDIENT

AVOBENZONE 3%

HOMOSALATE 15%

OCTISALATE 5%

OCTOCRYLENE 8%

PURPOSE

SUNSCREEN

USES

- HELPS PREVENT SUNSCREEN
- IF USED AS DIRECTED WITH OTHER SUN PROTECTION MEASURES (SEE DIRECTIONS), DECREASES THE RISK OF SKIN CANCER AND EARLY SKIN AGING CAUSED BY THE SUN.

WARNINGS

For external use only.

Flammable, keep away from heat and flame.

Do not useon damaged or broken skin.

Stop use and ask a doctorif rash occurs.

When using this product

- keep out of eyes. Rinse with water to remove.
- Do not puncture or incinerate. Contents under pressure. Do not store at temperatures above 120°F.

Keep out of reach of children.If swallowed, get medical help or contact a Poison Control Center immediately.

DIRECTIONS

- Apply liberally 15 minutes before sun exposure.
- Reapply: after 80 minutes of swimming or sweating
- immediately after towel drying
- at least every 2 hours.
- spray on hands to apply to face.
- use in well-ventilated area
- Children under 6 months: ask a doctor.

Sun Protection Measures.Spending time in the sun increases your risk of skin cancer and early skin aging. To decrease this risk, regularly use a sunscreen with a Broad Spectrum SPF 15 value or higher along with other sun protection measures including:

- limit time in the sun, especially from 10 a.m. – 2 p.m.
- wear long sleeved shirts, pants, hats and sunglasses.

OTHER INFORMATION

- Protect the product in this container from excessive heat and direct sun
- May stain surfaces and fabrics.

INACTIVE INGREDIENTS

ACRYLATES/OCTYLACRYLAMIDE COPOLYMER, ALOE BARBADENSIS LEAF JUICE, COCOS NUCIFERA (COCONUT) OIL, DIISOPROPYL ADIPATE, FRAGRANCE, SD ALCOHOL, TOCOPHERYL ACETATE.

QUESTIONS OR COMMENTS?

1- 626-599-3700Monday – Friday 9 AM – 5 PM PST